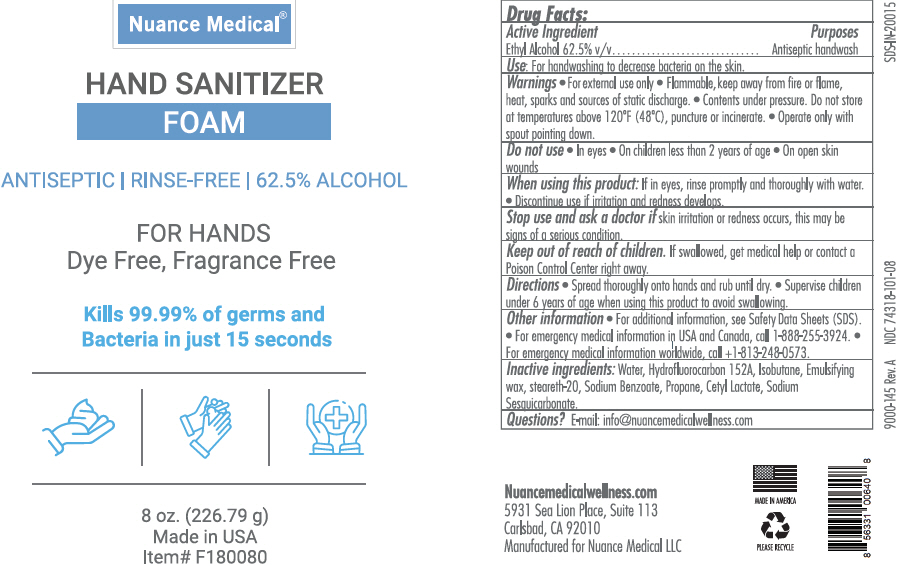 DRUG LABEL: Nuance Medical
NDC: 74318-101 | Form: AEROSOL, FOAM
Manufacturer: Nuance Medical, LLC
Category: otc | Type: HUMAN OTC DRUG LABEL
Date: 20210716

ACTIVE INGREDIENTS: ALCOHOL 54.7 g/100 g
INACTIVE INGREDIENTS: WATER; 1,1-DIFLUOROETHANE; ISOBUTANE; STEARETH-20; SODIUM BENZOATE; PROPANE; CETYL LACTATE; SODIUM SESQUICARBONATE

Nuance Medical®

Drug Facts

Active ingredient

Ethyl Alcohol 62.5% v/v

Purposes

Antiseptic handwash

Uses

for handwashing to decrease bacteria on the skin

Warnings

- For external use only
- Flammable, keep away from fire or flame, heat, sparks, and sources of static discharge
- Contents under pressure. Do not store at temperatures above 120°F (48°C), puncture or incinerate. For best foam density store and use at 55-85°F (13-29°C)
- Operate only with spout pointing down

Do not use

- In eyes or face.

When using this product

- If in eyes, rinse promptly and thoroughly with water
- Discontinue use if irritation and redness develops

Stop use and ask a doctor if skin irritation or redness occur for more than 72 hours.

Keep out of reach of children. If swallowed, get medical help or contact a Poison Control Center right away.

Directions

- Spread thoroughly onto hands and rub until dry.

Other Information

- For additional information, see Safety Data Sheets (SDS)
- For emergency medical information in USA and Canada, call 1-888-255-3924
- For emergency medical information worldwide, call 1-813-248-0573

Inactive Ingredients

Water. Hydrofluorocarbon 152A, Isobutane, Emulsifying wax, Steareth-20, Sodium Benzoate, Propane, Cetyl Lactate, Sodium Sesquicarbonate

Questions?

E-mail: info@nuancemedicalwellness.com

PRINCIPAL DISPLAY PANEL - 226.79 g Can Label

Nuance Medical®

HAND SANITIZER
FOAM

ANTISEPTIC | RINSE-FREE | 62.5% ALCOHOL

FOR HANDS
Dye Free, Fragrance Free

Kills 99.99% of germs and
Bacteria in just 15 seconds

8 oz. (226.79 g)
Made in USA
Item# F180080